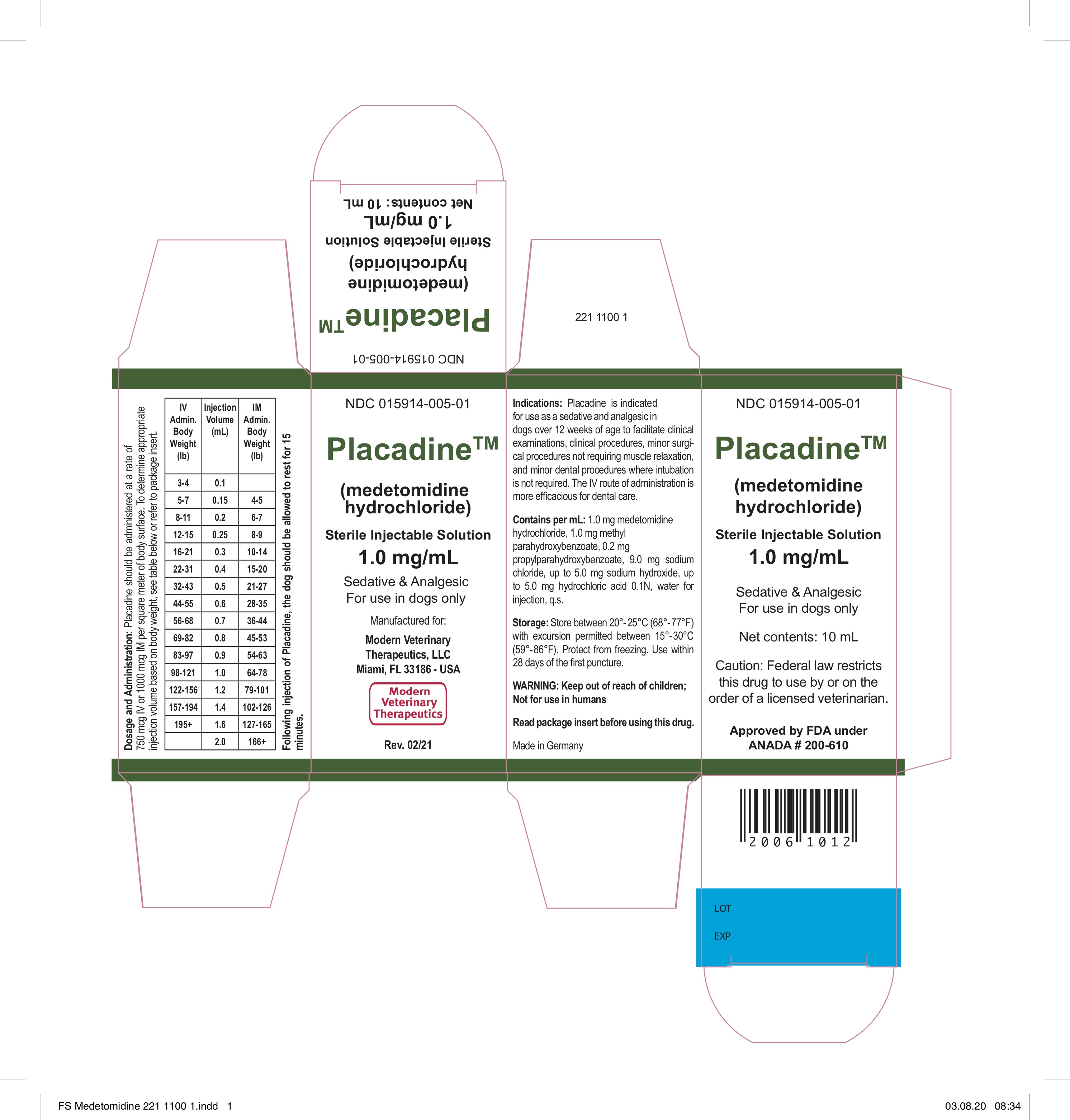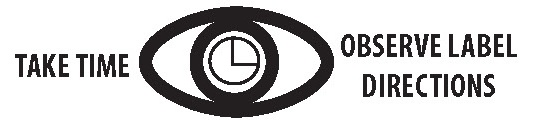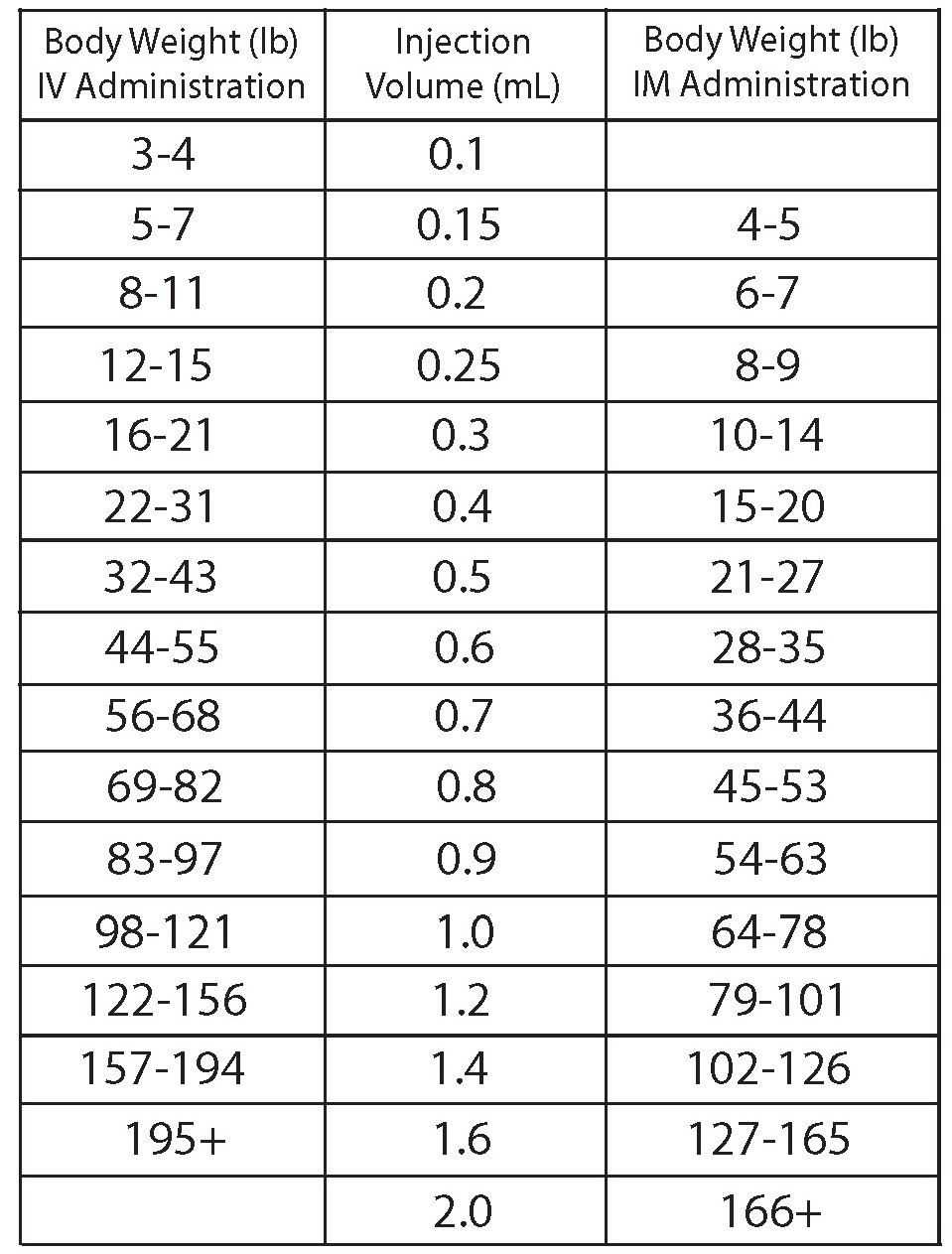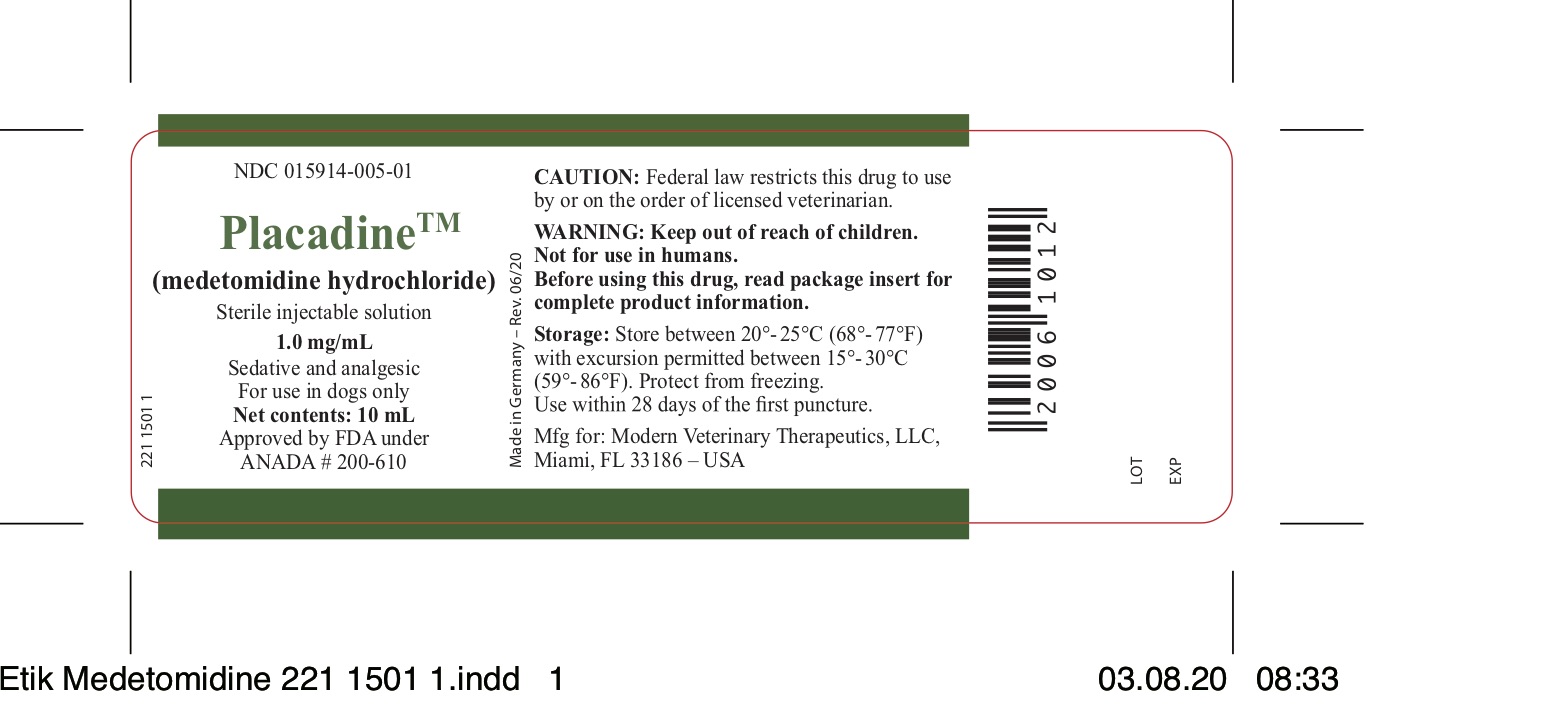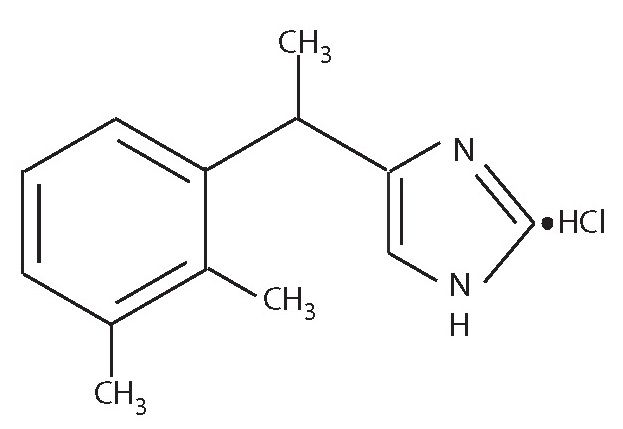 DRUG LABEL: Placadine
NDC: 15914-005 | Form: INJECTION, SOLUTION
Manufacturer: Modern Veterinary Therapeutics LLC
Category: animal | Type: PRESCRIPTION ANIMAL DRUG LABEL
Date: 20211209

ACTIVE INGREDIENTS: MEDETOMIDINE HYDROCHLORIDE 1 mg/1 mL
INACTIVE INGREDIENTS: METHYLPARABEN 1 mg/1 mL; PROPYLPARABEN 0.2 mg/1 mL; SODIUM CHLORIDE 9.0 mg/1 mL; HYDROCHLORIC ACID 5.0 mg/1 mL; SODIUM HYDROXIDE 5.0 mg/1 mL; WATER 1 mL/1 mL

Placadine™

Placadine™ (medetomidine hydrochloride)

Sterile Injectable Solution
1.0 mg/mL
Sedative and Analgesic
For intramuscular and intravenous use in dogs only

CAUTION

Federal law restricts this drug to use by or on the order of a licensed veterinarian.

DESCRIPTION

Placadine (medetomidine hydrochloride) is a synthetic α2-adrenoreceptor agonist with sedative and analgesic properties. The chemical name is (±)-4-[1-(2,3-dimethylphenyl)ethyl]-1H-imidazole monohydrochloride. It is a white, or almost white, crystalline, water soluble substance having a molecular weight of 236.7. The molecular formula is C13H16N2•HCl and the structural formula is:

Each mL of Placadine contains 1.0 mg medetomidine hydrochloride, 1.0 mg methyl parahydroxybenzoate, 0.2 mg propylparahydroxybenzoate, 9.0 mg sodium chloride, up to 5.0 mg sodium hydroxide, up to 5.0 mg hydrochloric acid 0.1N, water for injection, q.s.

CLINICAL PHARMACOLOGY

Medetomidine is a potent non-narcotic α2-adrenoreceptor agonist which produces sedation and analgesia. These effects are dose dependent in depth and duration. Profound sedation and recumbency, with reduced sensitivity to environmental stimuli (sounds, etc.), are seen with medetomidine.

The pharmacological restraint and pain relief provided by medetomidine facilitates handling dogs and aids in the conduct of diagnostic or therapeutic procedures. It also facilitates minor surgical procedures (with or without local anesthesia) and dental care where intubation is not required. Spontaneous muscle contractions (twitching) can be expected in some dogs sedated with medetomidine.

With medetomidine administration, blood pressure is initially increased due to peripheral vasoconstriction and thereafter drops to normal or slightly below normal levels. The initial vasopressor response is accompanied by a compensatory marked decrease in heart rate mediated by a vagal baroreceptor mechanism. The bradycardia may be partially prevented by prior (at least 5 minutes before) intravenous administration of an anticholinergic agent (see PRECAUTIONS). A transient change in the conductivity of the cardiac muscle may occur, as evidenced by atrioventricular blocks. Cardiovascular changes (such as profound bradycardia and second degree heart block) equally affect both heartworm negative and asymptomatic heartworm positive dogs.

Respiratory responses include an initial slowing of respiration within a few seconds to 1–2 minutes after administration, increasing to normal within 120 minutes. An initial decrease in tidal volume is followed by an increase. When medetomidine was given at 3 and 5 times the recommended dose IV, and 5 and 10 times IM, effects were not intensified but were prolonged.

INDICATIONS

Placadine is indicated for use as a sedative and analgesic in dogs over 12 weeks of age to facilitate clinical examinations, clinical procedures, minor surgical procedures not requiring muscle relaxation, and minor dental procedures where intubation is not required. The IV route of administration is more efficacious for dental care.

WARNINGS

Keep out of reach of children. Not for use in humans.

Medetomidine hydrochloride can be absorbed and may cause irritation following direct exposure to skin, eyes, or mouth. In case of accidental eye exposure, flush with water for 15 minutes. In case of accidental skin exposure, wash with soap and water. Remove contaminated clothing. If irritation or other adverse reaction occurs (e.g., sedation, hypotension, bradycardia), seek medical attention. In case of accidental oral exposure or injection, seek medical attention. Precaution should be used while handling and using filled syringes.

Users with cardiovascular disease (e.g., hypertension or ischemic heart disease) should take special precautions to avoid any exposure to this product.

The safety data sheet (SDS) contains more detailed occupational safety information. To report suspected adverse drug events, for technical assistance or to obtain a copy of the SDS, contact Modern Veterinary Therapeutics, LLC at 407-852-8039 or www.modernveterinarytherapeutics.com.

For additional information about adverse drug experience reporting for animal drugs, contact FDA at 1-888-FDA-VETS or online at www.fda.gov/reportanimalae

NOTE TO PHYSICIANS

This product contains an α2-adrenergic agonist.

CONTRAINDICATIONS

Placadine should not be used in dogs with the following conditions: cardiac disease, respiratory disorders, liver or kidney diseases, dogs in shock, dogs which are severely debilitated, or dogs which are stressed due to extreme heat, cold or fatigue.

PRECAUTIONS

In extremely nervous or excited dogs, levels of endogenous catecholamines are high due to the animal’s state of agitation. The pharmacological response elicited by α2-agonists (e.g., medetomidine) in such animals is often reduced, with depth and duration of sedative/analgesic effects ranging from slightly diminished to nonexistent. Highly agitated dogs should therefore be put at ease and allowed to rest quietly prior to receiving Placadine. Allowing dogs to rest quietly for 10 to 15 minutes after injection may improve the response to Placadine.

In dogs not responding satisfactorily to treatment with Placadine, repeat dosing is not recommended. Caution should be exercised when handling sedated animals. Handling or any other sudden stimuli may cause a defense reaction in an animal that is sedated.

Placadine is a potent α2-agonist which should be used with caution with other sedative or analgesic drugs. Additive or synergistic effects are likely, possibly resulting in overdose. Although bradycardia may be partially prevented by prior (at least 5 minutes before) intravenous administration of an anticholinergic agent, the administration of anticholinergic agents to treat bradycardia either simultaneously with medetomidine or following sedation with medetomidine could lead to adverse cardiovascular effects.

Special care is recommended when treating very young animals and older animals. Information on the possible reproductive effects of medetomidine is limited; therefore, the drug is not recommended for use in dogs used for breeding purposes or in pregnant dogs.

ADVERSE REACTIONS

As with all α2-agonists, the potential for isolated cases of hypersensitivity, including paradoxical response (excitation), exists. Incidents of prolonged sedation, bradycardia, cyanosis, vomiting, apnea, death from circulatory failure with severe congestion of lungs, liver, kidney and recurrence of sedation after initial recovery have been reported.

SIDE EFFECTS

Bradycardia with occasional atrioventricular blocks will occur together with decreased respiratory rates. Body temperature is slightly or moderately decreased. Urination typically occurs during recovery at about 90 to 120 minutes posttreatment. In approximately 10% of treated dogs, occasional episodes of vomiting occur between 5 to 15 minutes posttreatment. An increase in blood glucose concentration is seen due to α2-adrenoreceptor-mediated inhibition of insulin secretion.

ANIMAL SAFETY

In target animal safety studies, medetomidine was tolerated in dogs at up to 5 times the recommended IV dose and up to 10 times the recommended IM dose. A single IV administration of 10 times the recommended dose in dogs caused a prolonged anesthesia-like condition accompanied by an increased level of spontaneous muscle contractions (twitching). Repeated IV doses of 3 or 5 times the recommended dose caused a profound sedation, bradycardia, and reduced respiratory rates over several hours, accompanied in some animals by occasional spontaneous twitching. Death (approximately 1 in 40,000 treatments) has been noted in clinical use with doses at 2 times the recommended dose of medetomidine hydrochloride.

DOSAGE AND ADMINISTRATION

Placadine should be administered at the rate of 750 mcg IV or 1000 mcg IM per square meter of body surface. Use the table below to determine the correct dosage on the basis of body weight.

Following injection of Placadine, the dog should be allowed to rest quietly for 15 minutes.

STORAGE

Store between 20°- 25°C (68°- 77°F) with excursion permitted between 15°- 30°C (59°- 86°F).
Protect from freezing. Use within 28 days of the first puncture.

HOW SUPPLIED

Placadine is supplied in 10-mL, multidose vials containing 1.0 mg of medetomidine hydrochloride per mL.
NDC 015914-005-01 - 10 mL vials

Approved by FDA under ANADA # 200-610